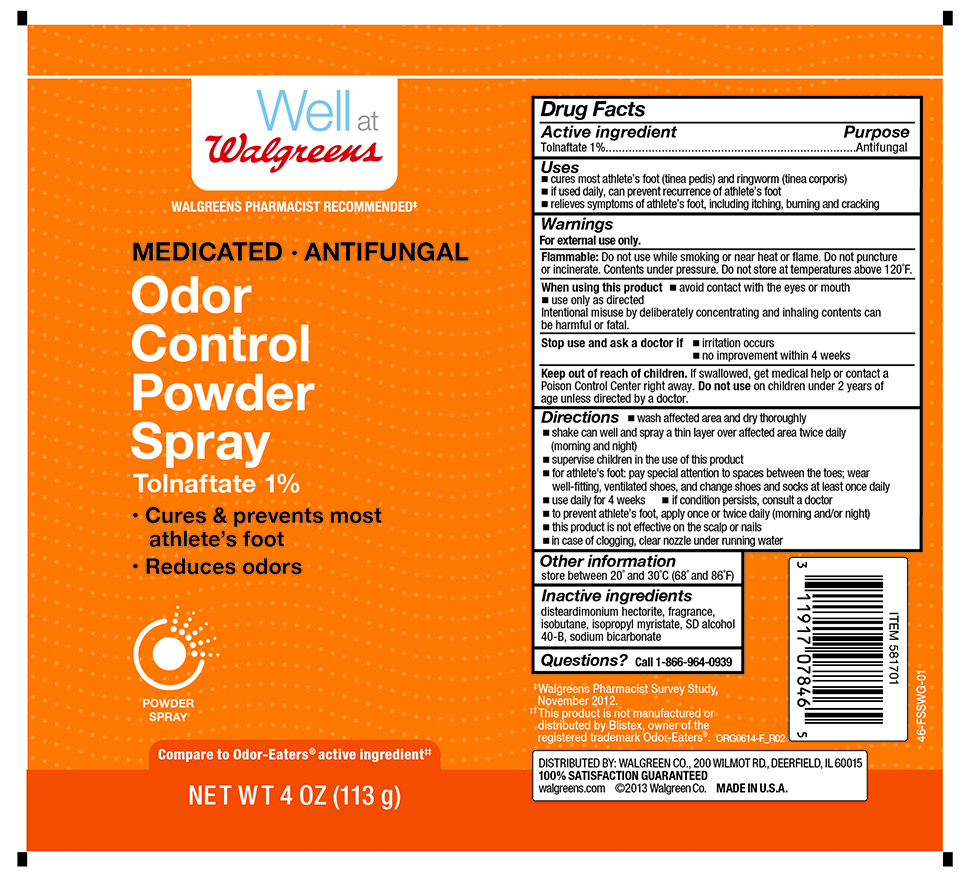 DRUG LABEL: Tolnaftate
NDC: 0363-0216 | Form: AEROSOL, SPRAY
Manufacturer: Walgreen Company
Category: otc | Type: HUMAN OTC DRUG LABEL
Date: 20251216

ACTIVE INGREDIENTS: TOLNAFTATE 1.3 g/113 g
INACTIVE INGREDIENTS: ISOPROPYL MYRISTATE; DISTEARDIMONIUM HECTORITE; ISOBUTANE; ALCOHOL; SODIUM BICARBONATE

Walgreens Odor Control Powder Spray

Active ingredient

Tolnaftate 1%

Purpose

Antifungal

Uses

- prevents recurrence of athlete's foot with daily use
- cures mose athlete's foot (tinea pedis) and ringworm (tinea corporis)
- relieves sypmtoms of athlete's foot, including itching, burning and cracking

Warnings

For external use only.

Flammable:

Do not use while smoking or near heat or flame. Do not puncture or incinerate. Contents under pressure. Don not store at temperatures above 120^0F.

When using this product

- avoid contact with the eyes or mouth
- use only as directed
- Intentional misuse by deliberately concentrating and inhaling contents can be harmful or fatal.

Stop use and ask a doctor if

- irritation occurs
- no improvement within 4 weeks

Keep out of reach of children.

If swallowed, get medical help or contact a Poison Control Center right away. Do not use on children under 2 years of age unless directed by a doctor.

Directions

- wash affected area and dry thoroughly
- shake can well and spray a thin layer over affected area twice daily (morning and night)
- supervise children in the use of this product
- for athlete's foot: pay special attention to spaces between the toes; wear well-fitting, ventilated shoes, and change shoes and socks at least once daily
- use daily for 4 weeks
- if condition persists, consult a doctor
- to prevent athlete's foot, apply once or twice daily (morning and/or night)
- this product is not effective on the scalp or nails
- in case of clogging, clear nozzle under running water

Other information

store between 20º and 30ºC (68º and 86ºF)

Inactive ingredients

disteardimonium hectorite, fragrance, isobutane, isopropyl myristate, SD alcohol 40-B, sodium bicarbonate

Questions?

call 1-866-964-0939

RECENT MAJOR CHANGES

..

Principal Display Panel

Well at Walgreens

MEDICATED . ANTIFUNGAL

ODOR

CONTROL

POWDER

SPRAY

Tolnaftate 1%

- Cures & prevents most

athlete's foot

- Reduces odors

NET WT 4 OZ (113 g)